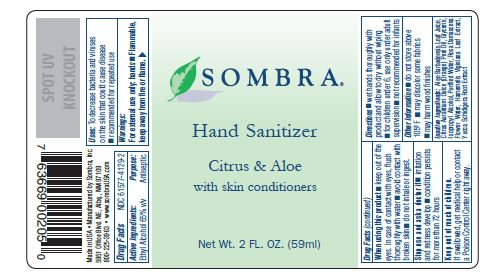 DRUG LABEL: Sombra Hand Sanitzer
NDC: 61577-4129 | Form: SPRAY
Manufacturer: SOMBRA COSMETICS
Category: otc | Type: HUMAN OTC DRUG LABEL
Date: 20200722

ACTIVE INGREDIENTS: ALCOHOL 65 mL/100 mL
INACTIVE INGREDIENTS: ALOE VERA LEAF; ORANGE PEEL; GLYCERIN; WITCH HAZEL; ISOPROPYL ALCOHOL; WATER; ROSA DAMASCENA FLOWER; YUCCA SCHIDIGERA ROOT

Sombra Hand Sanitizer

Active Ingredient

Ethyl Alcohol 65%

Purpose

Antiseptic

Uses

To decrease bacteria and viruses on the skin that could cause disease. Recommended for repeated use.

Warnings

Flammable. Keep away from fire or flame. For external use only: hands.

Do not use

Stop use and ask doctor if, irritation and redness develop condition persists for more than 72 hours.

When using this product, keep out of the eyes. In case of contact with eyes, flush thoroughly with water. Avoid contact with broken skin. Do not inhale or ingest.

Stop use and ask a doctor

Stop use and ask doctor if, irritation and redness develop condition persists for more than 72 hours.

Keep out of reach of children

If swallowed, get medical help or contact a Poison Control Center right away.

Directions

Wet hands thoroughly with product and allow to dry without wiping. For children under 6, use only under adult supervision. Not recommended for infants.

Other Information

Do not store above 105F. May discolor some fabrics. May harm wood finishes.

Inactive ingredients

Aloe Barbadensis leaf juice, Citrus Aurantium Dulce (orange) Peel Oil, Glycerin, Isopropyl Alcohol, Purified Water, Rosa Damascena Flower Water, Hamemelis Viginiara Leaf Extract, Yucca Schidigera Root Extract.